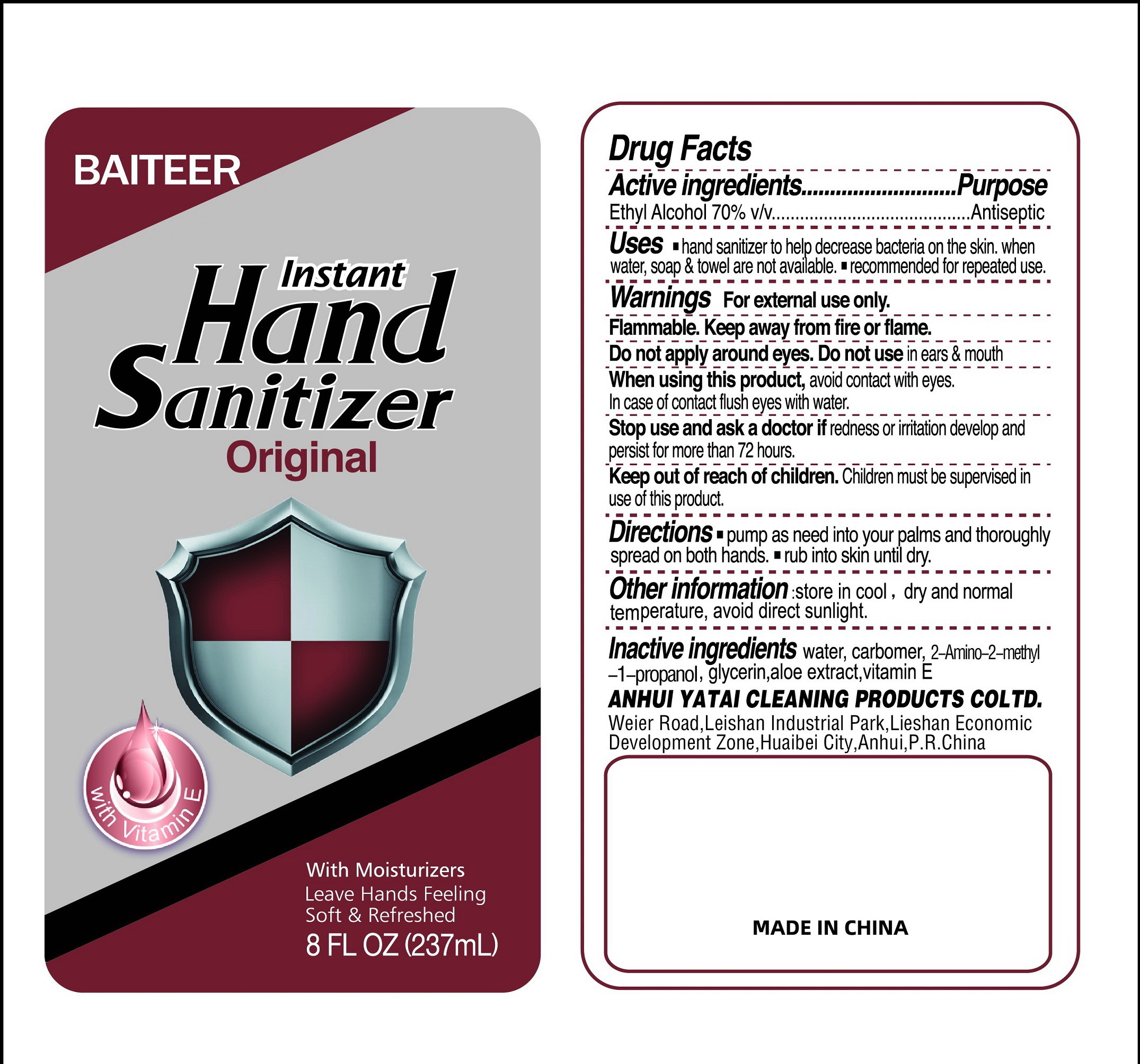 DRUG LABEL: BAITEER Instant Hand Sanitizer Original
NDC: 76797-001 | Form: SOLUTION
Manufacturer: Anhui Yatai Cleaning Products Co., Ltd.
Category: otc | Type: HUMAN OTC DRUG LABEL
Date: 20200528

ACTIVE INGREDIENTS: ALCOHOL 70 mL/100 mL
INACTIVE INGREDIENTS: GLYCERIN; CARBOMER 934; .ALPHA.-TOCOPHEROL ACETATE; ALOE VERA WHOLE; AMINOMETHYL PROPANEDIOL

Active Ingredient(s)

Ethyl Alcohol 70% v/v

Purpose

Antiseptic

Use

Hand sanitizer to help decrease bacteria on the skin when water, soap and towel are not available

Recommended for repeated use

Warnings

For external use only. Flammable. Keep away from fire or flame

Do not apply around eyes, do not use in ears and mouth

When using this product aviod contact with eyes. In case of contact, flush eyes with water.

Stop use and ask a doctor if irritation or redness develop and last for more than 72 hours

Keep out of reach of children. Children must be supervised in use of this product.

Directions

Pump as needed into your palms and thoroughly spread on both hands

Rub into skin until dry

Inactive ingredients

Water, Carbomer, Aminomethyl Propanol, Aloe Vera extract, Vitamin E

Other Information:

Store in cool, dry, and normal temperature

Aviod direct sunlight